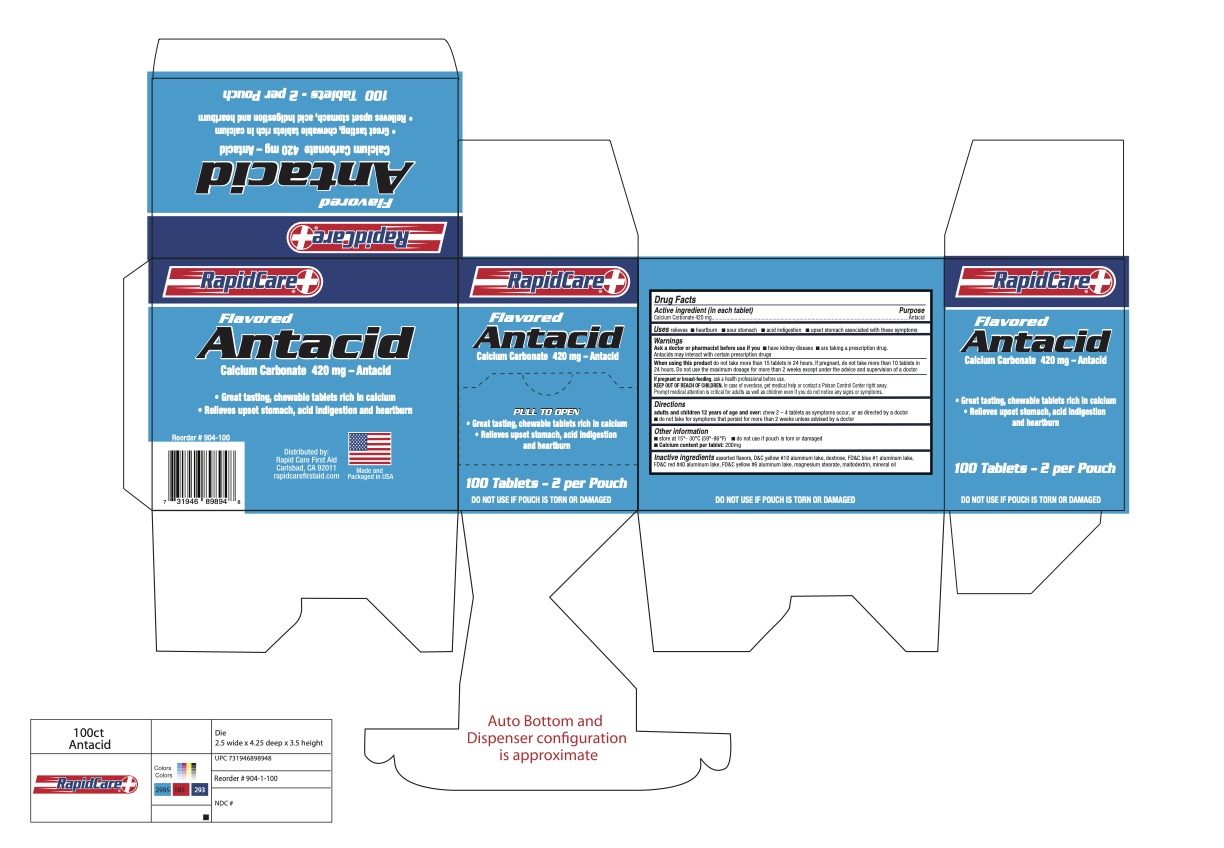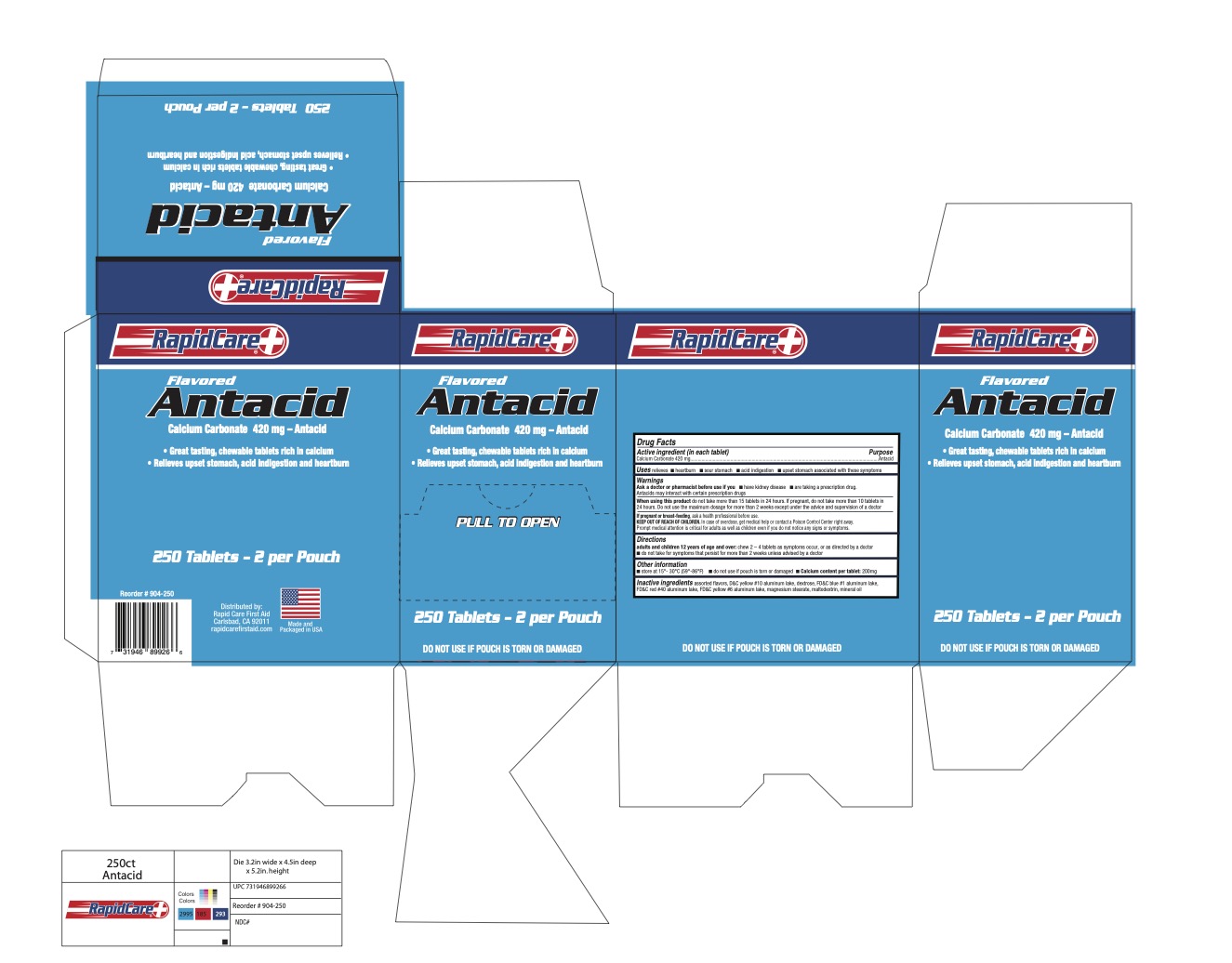 DRUG LABEL: RapidCare Flavored Antacid
NDC: 73659-015 | Form: TABLET, CHEWABLE
Manufacturer: Rapid Care, Inc
Category: otc | Type: HUMAN OTC DRUG LABEL
Date: 20220418

ACTIVE INGREDIENTS: CALCIUM CARBONATE 420 mg/1 1
INACTIVE INGREDIENTS: DEXTROSE; MALTODEXTRIN; FD&C RED NO. 40; MAGNESIUM STEARATE

RapidCare - Antacid 420mg

Active ingredient (in each tablet)

Calcium Carbonate 420 mg

PURPOSE

Antacid

Uses

relieves

- heartburn
- sour stomach
- acid indigestion
- upset stomach associated with these symptoms

Ask a doctor or pharmacist before use if you

- have kidney disease
- are taking a prescription drug.

Antacids may interact with certain prescription drugs

When using this product do not take more than 15 tablets in 24 hours. If pregnant, do not take more than 10 tablets in

24 hours. Do not use the maximum dosage for more than 2 weeks except under the advice and supervision of a doctor

PREGNANCY OR BREAST FEEDING

If pregnant or breast-feeding, ask a health professional before use.

KEEP OUT OF REACH OF CHILDREN. In case of overdose, get medical help or contact a Poison Control Center right away.

Prompt medical attention is critical for adults as well as children even if you do not notice any signs or symptoms.

DOSAGE AND ADMINISTRATION

adults and children 12 years of age and over: chew 2 – 4 tablets as symptoms occur, or as directed by a doctor

do not take for symptoms that persist for more than 2 weeks unless advised by a doctor

Other information

- store at 15°- 30°C (59°-86°F)
- do not use if pouch is torn or damaged
- Calcium content per tablet: 200mg

INACTIVE INGREDIENT

assorted flavors, D&C yellow #10 aluminum lake, dextrose, FD&C blue #1 aluminum lake, FD&C red #40 aluminum lake, FD&C yellow #6 aluminum lake, magnesium stearate, maltodextrin, mineral oil